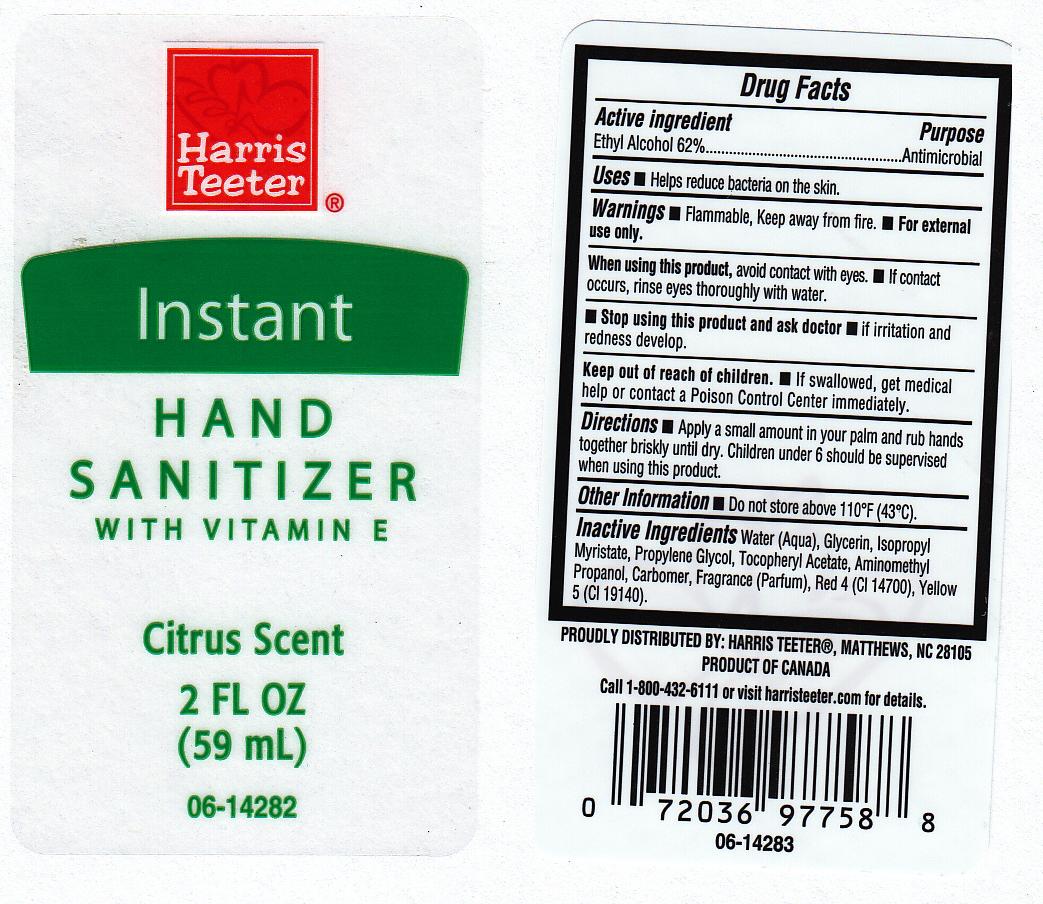 DRUG LABEL: INSTANT HAND SANITIZER
NDC: 72036-230 | Form: GEL
Manufacturer: HARRIS TEETER
Category: otc | Type: HUMAN OTC DRUG LABEL
Date: 20111025

ACTIVE INGREDIENTS: ALCOHOL 62 mL/100 mL
INACTIVE INGREDIENTS: WATER; GLYCERIN; ISOPROPYL MYRISTATE; PROPYLENE GLYCOL; .ALPHA.-TOCOPHEROL ACETATE, D-; AMINOMETHYLPROPANOL; CARBOMER 934; FD&C RED NO. 4; FD&C YELLOW NO. 5

DRUG FACTS

ACTIVE INGREDIENT

ETHYL ALCOHOL 62%

PURPOSE

ANTIMICROBIAL

USES

HELPS REDUCE BACTERIA ON THE SKIN.

WARNINGS

- FLAMMABLE, KEEP AWAY FROM FIRE.
- FOR EXTERNAL USE ONLY.

WHEN USING THIS PRODUCT

AVOID CONTACT WITH EYES. IF CONTACT OCCURS, RINSE EYES THROUGHLY WITH WATER.

STOP USING THIS PRODUCT AND ASK DOCTOR

IF IRRITATION AND REDNESS DEVELOP.

KEEP OUT OF REACH OF CHILDREN

IF SWALLOWED, GET MEDICAL HELP OR CONTACT A POISON CONTROL CENTER IMMEDIATELY.

DIRECTIONS

APPLY A SMALL AMOUNT IN YOUR PALM AND RUB HANDS TOGETHER BRISKLY UNTIL DRY. CHILDREN UNDER 6 SHOULD BE SUPERVISED WHEN USING THIS PRODUCT.

OTHER INFORMATION

DO NOT STORE ABOVE 110 DEGREES FAHRENHEIT (43 DEGREES CELSIUS).

INACTIVE INGREDIENTS

WATER (AQUA), GLYCERIN, ISOPROPYL MYRISTATE, PROPYLENE GLYCOL, TOCOPHERYL ACETATE, AMINOMETHYL PROPANOL, CARBOMER, FRAGRANCE, RED 4 (CI 14700), YELLOW 5 (CI 19140).